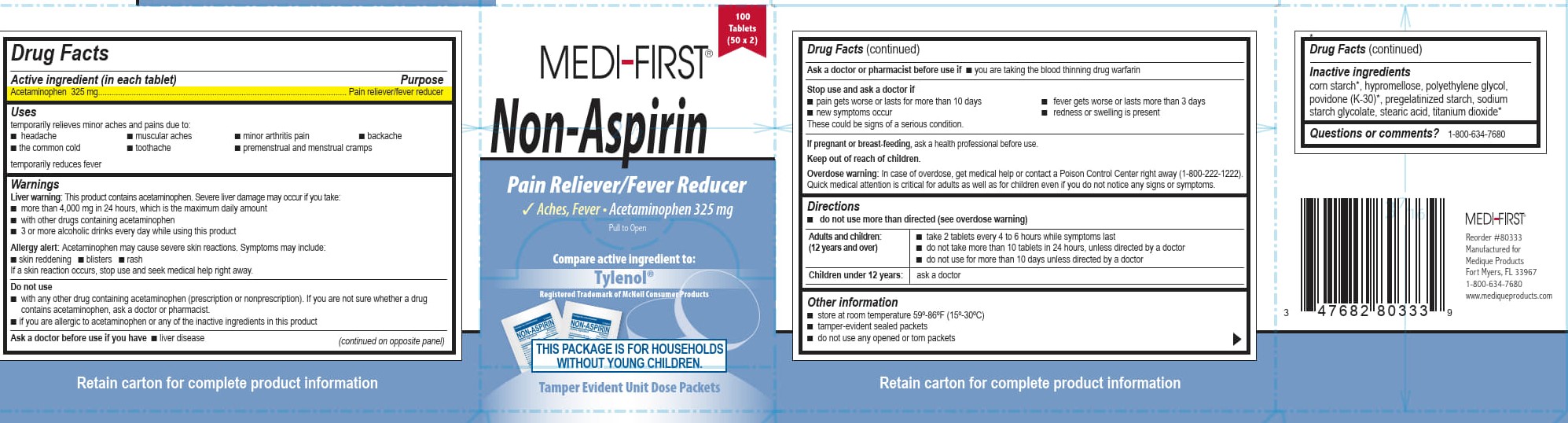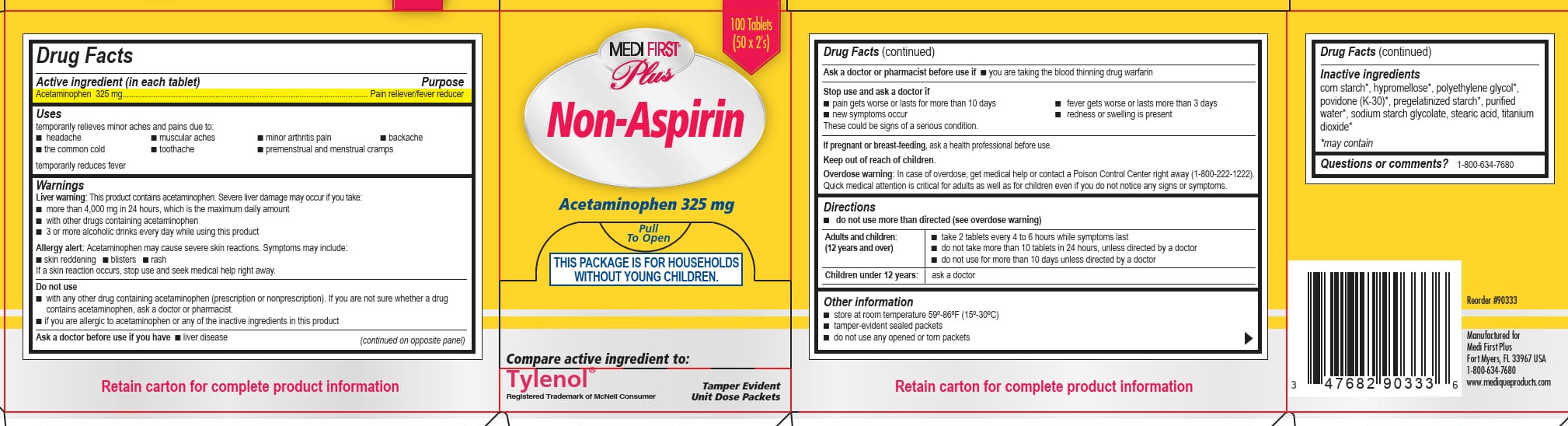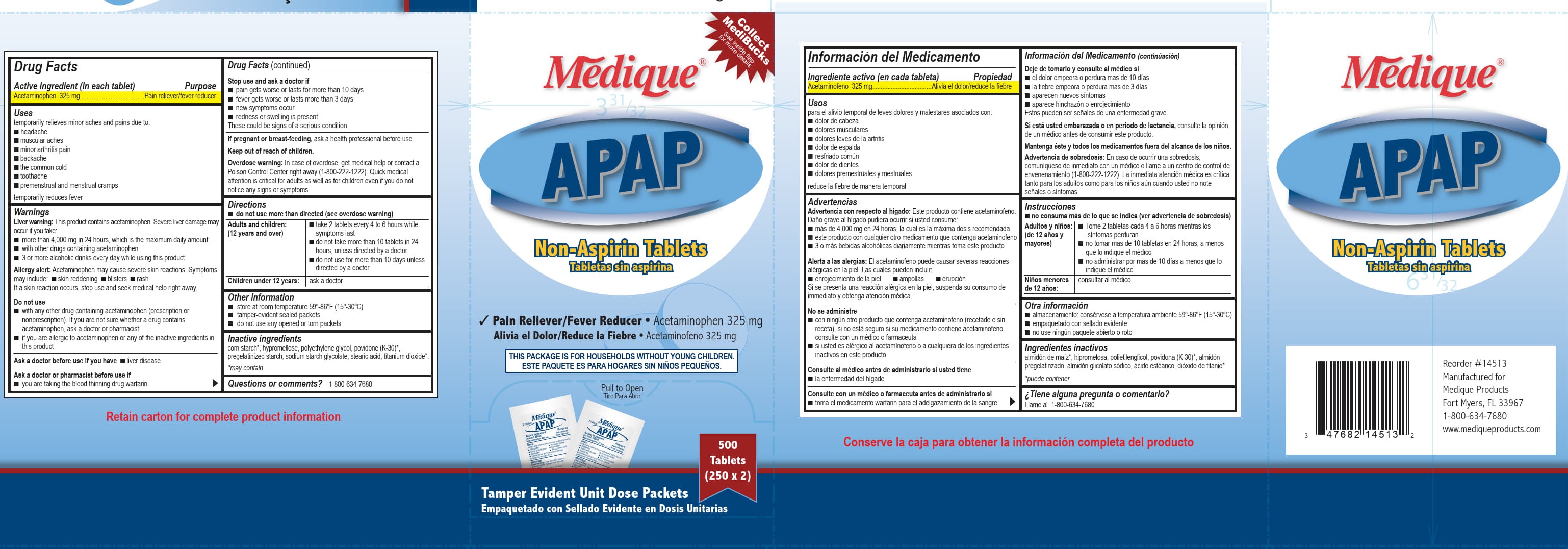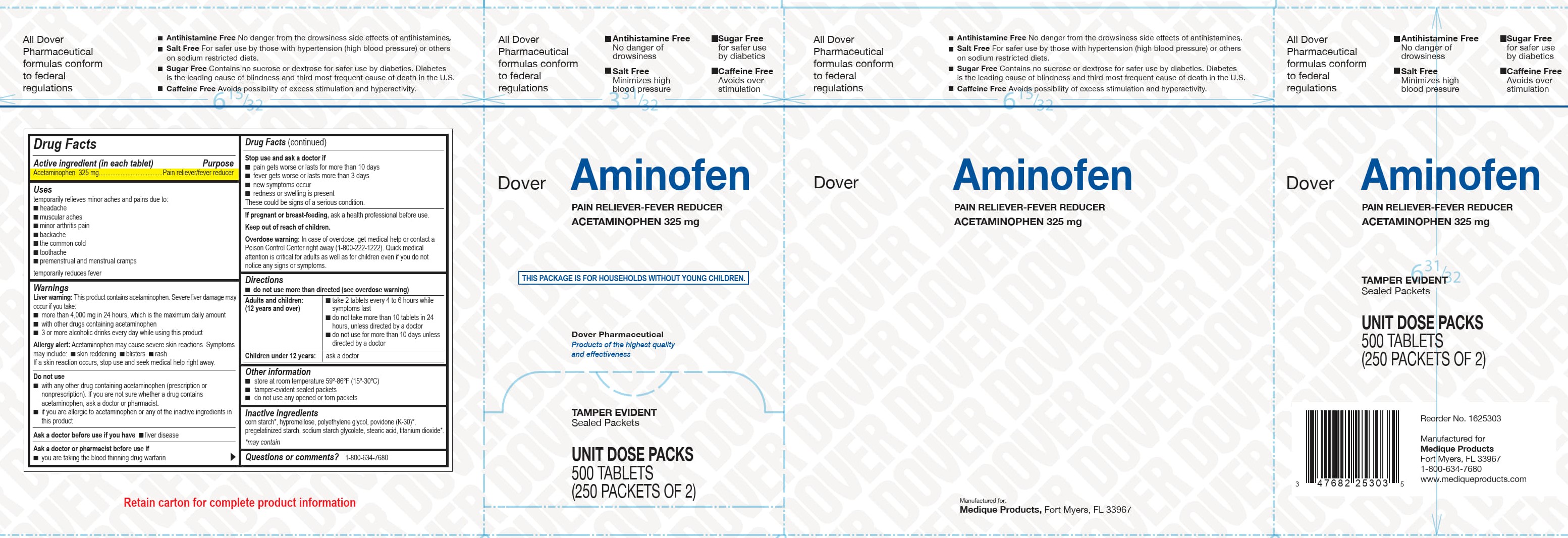 DRUG LABEL: Medi-First Non-Aspirin
NDC: 47682-058 | Form: TABLET, COATED
Manufacturer: Unifirst First Aid Corporation
Category: otc | Type: HUMAN OTC DRUG LABEL
Date: 20250908

ACTIVE INGREDIENTS: ACETAMINOPHEN 325 mg/1 1
INACTIVE INGREDIENTS: HYPROMELLOSE, UNSPECIFIED; SODIUM STARCH GLYCOLATE TYPE A POTATO; STEARIC ACID; POLYETHYLENE GLYCOL, UNSPECIFIED; POVIDONE K30; STARCH, CORN

Acetaminophen 325 mg

Drug Facts

Active ingredient (in each tablet)

Acetaminophen 325 mg

Purpose

Pain reliever/fever reducer

Uses

temporarily relieves minor aches and pains due to:

- headache
- muscular aches
- minor arthritis pain
- backache
- the common cold
- toothache
- premenstrual and menstrual cramps

temporarily reduces fever

Warnings

Liver warning: This product contains acetaminophen. Severe liver damage may occur if you take:

- more than 4,000 mg in 24 hours, which is the maximum daily amount
- with other drugs containing acetaminophen
- 3 or more alcoholic drinks every day while using this product

Allergy alert:

Acetaminophen may cause severe skin reactions. Symptoms may include:

- skin reddening
- blisters
- rash

If a skin reaction occurs, stop use and seek medical help right away.

Do not use

- with any other drug containing acetaminophen (prescription or nonprescription). If you are not sure whether a drug contains acetaminophen, ask a doctor or pharmacist.
- if you are allergic to acetaminophen or any of the inactive ingredients in this product

Ask a doctor before use if you have

- liver disease

Ask a doctor or pharmacist before use if

- you are taking the blood thinning drug warfarin

Stop using and ask a doctor if

- pain gets worse and lasts for more than 10 days
- fever gets worse or lasts for more than 3 days
- new symptoms occur
- redness or swelling is present

These could be signs of a serious condition

PREGNANCY OR BREAST FEEDING

If pregnant or breast-feeding, ask a health professional before use.

Keep out of reach of children.

Overdose Warning:

In case of overdose, get medical help or contact a Poison Control Center right away (1-800-222-1222). Quick medical attention is critical for adults as well as for children even if you do not notice any signs or symptoms.

Directions

- do not use more than directed (see overdose warning)

Adults and children: (12 years and over)

- take 2 tablets every 4 to 6 hours while symptoms last.
- do not take more than 10 tablets in 24 hours, unless directed by a doctor
- do not use for more than 10 days unless directed by a doctor

Children under 12 years:

- ask a doctor

Other information

- store at room temperature 59°-86°F (15°-30°C)
- tamper-evident sealed packets
- do not use any opened or torn packets

Inactive ingredients

corn starch*, hypromellose, polyethylene glycol, povidone (K-30)*, pregelatinized starch, sodium starch glycolate, stearic acid, titanium dioxide*

May contain*

Questions or comments? 1-800-634-7680

Medique Apap

Medique ®

APAP

Non-Aspirin Tablets

Tabletas sin aspirina

Pain Reliever/Fever Reducer • Acetaminophen 325 mg

Alivia el Dolor/Reduce la Fiebre • Acetaminofeno 325 mg

This Package is For Households Without young Children

Este Paquete es Para Hogares sin Ninos Pequenos

Pull to Open

Tira Para Abrir

500 Tablets

(250 x 2)

Tamper Evident Unit Dose Packets

Empaquetado con Sellado Evidente en Dosis Unitarias

Medi-First Non Aspirin

Medi-First ®

Non-Aspirin

Pain Reliever/Fever Reducer

Aches, Fever ● Acetaminophen 325 mg

Compare active ingredient to:

Tylenol®

This Package is For Households Without Young Children

Tamper Evident Unit Dose Packets

100 Tablets

(50 x 2)

Medi-First Plus Non Aspirin

Medi First ® Plus

Non-Aspirin

Acetaminophen 325mg

Pull to Open

This Package is For Households Without Young Children

Pain Reliever/Fever Reducer

Compare active ingredient to:

Tylenol®

Registered Trademark of McNeil Consumer

Tamper Evident Unit Dose Packets

100 Tablets

(50 x 2's)

Dover Aminofen

Acetaminophen 325 MG

Pain Reliever-Fever Reducer

This Package is for Households withoutn Young Children.

Dover Pharmaceutical

Products of the highest quality and effectiveness

Tamper Evident

Sealed Packets

Unit Dose Packs

500 Tablets

(250 Packets of 2)

All Dover Pharmaceutical formulas conform to federal regulations

Antihistamine free

No danger of drowsiness

Sugar Free

for safer use by diabetics

Salt free

Minimizes high blood pressure

Caffeine Free

Avoides over stimulation